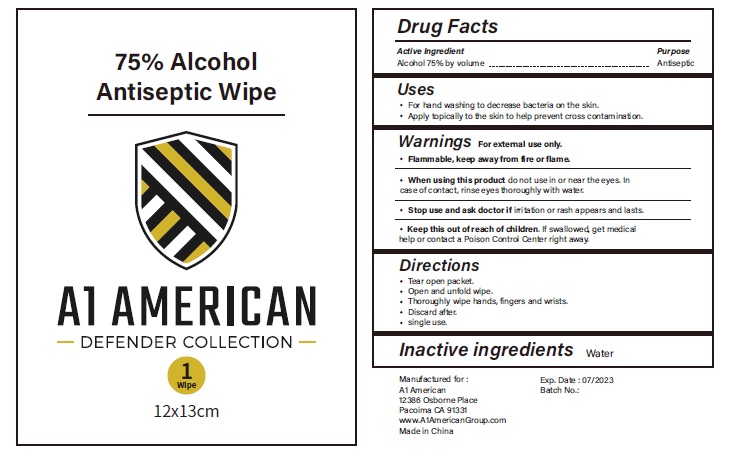 DRUG LABEL: A1 American Defender Collection
NDC: 78940-003 | Form: CLOTH
Manufacturer: Tiger Hospitality, LLC dba A1 American
Category: otc | Type: HUMAN OTC DRUG LABEL
Date: 20221227

ACTIVE INGREDIENTS: ALCOHOL 75 mL/100 mL
INACTIVE INGREDIENTS: GLYCERIN; HYDROGEN PEROXIDE; WATER

Active Ingredient(s)

Alcohol 75 % v/v.

Purpose

Antiseptic

Uses

For hand washing to decrease bacteria on the skin.

Apply topically to the skin to help prevent cross contamination

Warnings

For external use only. Flammable. Keep away from fire or flame

When using this product do not use in or near the eyes. In case of contact with eyes, rinse eyes thoroughly with water.

Stop use and ask a doctor if irritation or rash appears and lasts.

Keep out of reach of children. If swallowed, get medical help or contact a Poison Control Center right away.

Directions

Tear open packet

Open and unfold wipe

Thoroughly wipe hands, fingers and wrists

Discard after

single use

Inactive ingredient

Water